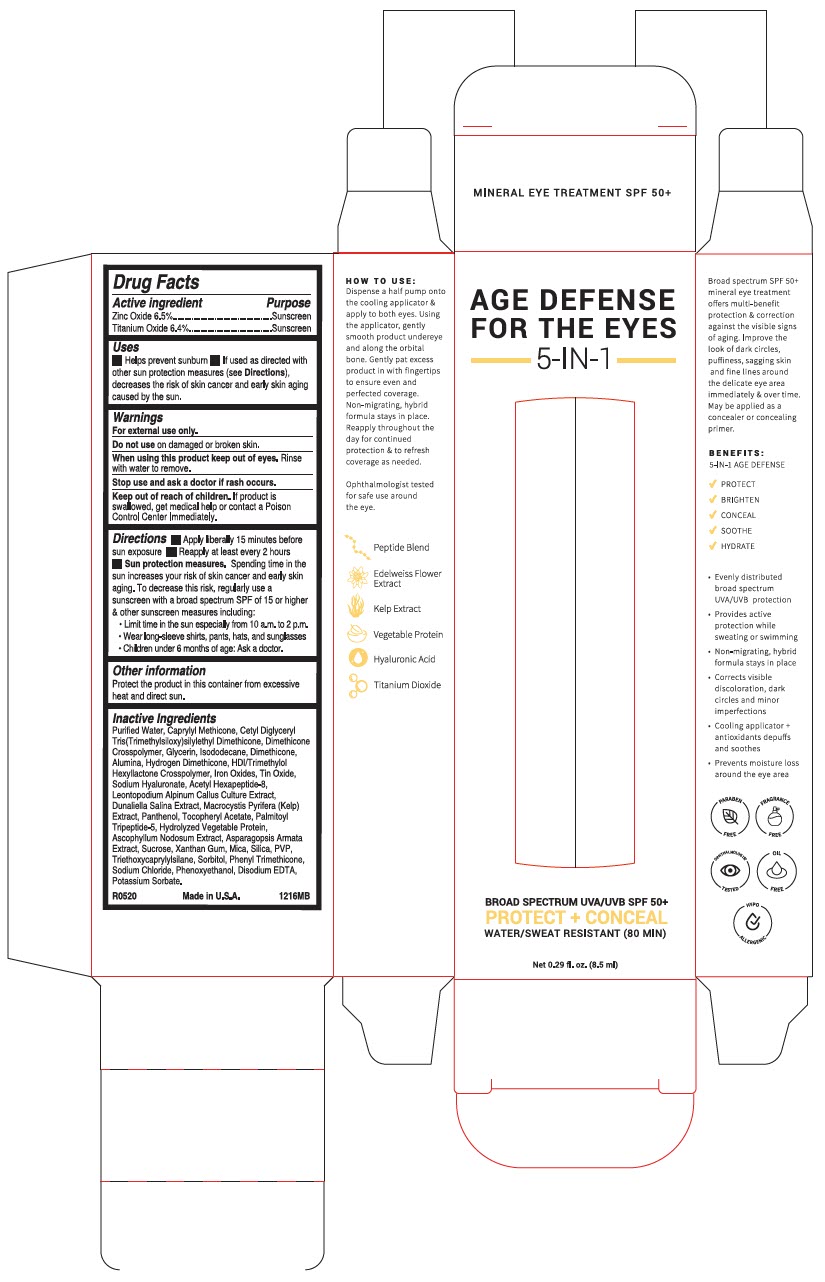 DRUG LABEL: Age Defense for Eyes
NDC: 51326-126 | Form: LOTION
Manufacturer: Topiderm, Inc.
Category: otc | Type: HUMAN OTC DRUG LABEL
Date: 20250603

ACTIVE INGREDIENTS: ZINC OXIDE 65 mg/1 mL; TITANIUM DIOXIDE 64 mg/1 mL
INACTIVE INGREDIENTS: WATER; CAPRYLYL TRISILOXANE; CETYL DIGLYCERYL TRIS(TRIMETHYLSILOXY)SILYLETHYL DIMETHICONE (3500 MM2/S); DIMETHICONE CROSSPOLYMER (450000 MPA.S AT 12% IN CYCLOPENTASILOXANE); GLYCERIN; ISODODECANE; DIMETHICONE; ALUMINUM OXIDE; HYDROGEN DIMETHICONE (45 CST); HEXAMETHYLENE DIISOCYANATE/TRIMETHYLOL HEXYLLACTONE CROSSPOLYMER; FERRIC OXIDE RED; STANNIC OXIDE; HYALURONATE SODIUM; ACETYL HEXAPEPTIDE-8 AMIDE; DUNALIELLA SALINA; MACROCYSTIS PYRIFERA; PANTHENOL; .ALPHA.-TOCOPHEROL ACETATE; PALMITOYL TRIPEPTIDE-5; ASCOPHYLLUM NODOSUM; ASPARAGOPSIS ARMATA; SUCROSE; XANTHAN GUM; MICA; SILICON DIOXIDE; POVIDONE, UNSPECIFIED; TRIETHOXYCAPRYLYLSILANE; SORBITOL; PHENYL TRIMETHICONE; SODIUM CHLORIDE; PHENOXYETHANOL; EDETATE DISODIUM; POTASSIUM SORBATE

Age Defense for Eyes
5 in 1

Drug Facts

ACTIVE INGREDIENT

Active ingredient | Purpose
Zinc Oxide 6.5% | Sunscreen
Titanium Oxide 6.4% | Sunscreen

Uses

- Helps prevent sunburn
- If used as directed with other sun protection measures (see Directions), decreases the risk of skin cancer and early skin aging caused by the sun.

Warnings

For external use only.

Do not use on damaged or broken skin.

When using this product keep out of eyes. Rinse with water to remove.

Stop use and ask a doctor if rash occurs.

Keep out of reach of children. If product is swallowed, get medical help or contact a Poison Control Center Immediately.

Directions

- Apply liberally 15 minutes before sun exposure
- Reapply at least every 2 hours
- Sun protection measures. Spending time in the sun increases your risk of skin cancer and early skin aging. To decrease this risk, regularly use a sunscreen with a broad spectrum SPF of 15 or higher & other sunscreen measures including:
  - Limit time in the sun especially from 10 a.m. to 2 p.m.
  - Wear long-sleeve shirts, pants, hats, and sunglasses
  - Children under 6 months of age: Ask a doctor.

Other information

Protect the product in this container from excessive heat and direct sun.

Inactive Ingredients

Purified Water, Caprylyl Methicone, Cetyl Diglyceryl Tris(Trimethylsiloxy)silylethyl Dimethicone, Dimethicone Crosspolymer, Glycerin, Isododecane, Dimethicone, Alumina, Hydrogen Dimethicone, HDI/Trimethylol Hexyllactone Crosspolymer, Iron Oxides, Tin Oxide, Sodium Hyaluronate, Acetyl Hexapeptide-8, Leontopodium Alpinum Callus Culture Extract, Dunaliella Salina Extract, Macrocystis Pyrifera (Kelp) Extract, Panthenol, Tocopheryl Acetate, Palmitoyl Tripeptide-5, Hydrolyzed Vegetable Protein, Ascophyllum Nodosum Extract, Asparagopsis Armata Extract, Sucrose, Xanthan Gum, Mica, Silica, PVP, Triethoxycaprylylsilane, Sorbitol, Phenyl Trimethicone, Sodium Chloride, Phenoxyethanol, Disodium EDTA, Potassium Sorbate.

PRINCIPAL DISPLAY PANEL - 8.5 ml Tube Box

AGE DEFENSE
FOR THE EYES
5-IN-1

BROAD SPECTRUM UVA/UVB SPF 50+
PROTECT + CONCEAL
WATER/SWEAT RESISTANT (80 MIN)

Net 0.29 fl. oz. (8.5 ml)